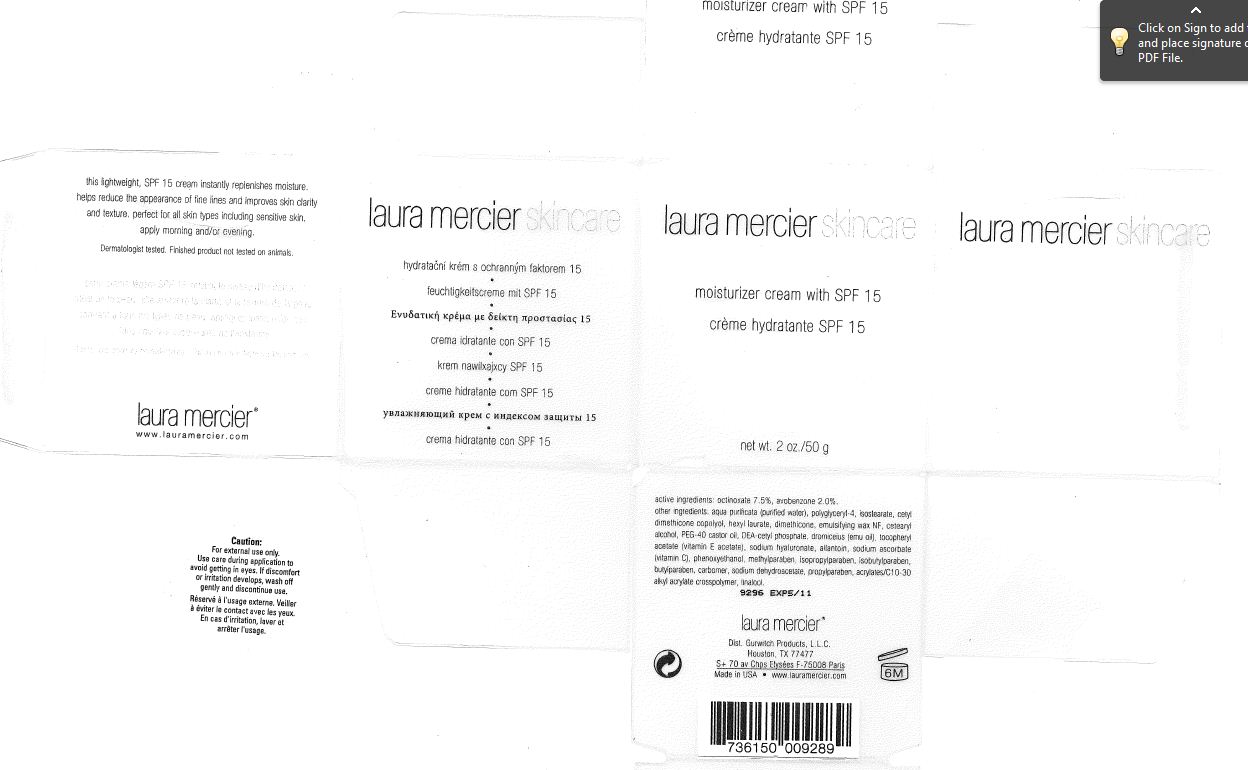 DRUG LABEL: Laura mercier  Moisturizer  cream with SPF 15
NDC: 65342-0947 | Form: CREAM
Manufacturer: Gurwitch Products, L.L.C.
Category: otc | Type: HUMAN OTC DRUG LABEL
Date: 20110502

ACTIVE INGREDIENTS: Octinoxate 3.75 g/50 g; Avobenzone 1 g/50 g
INACTIVE INGREDIENTS: Water; Dimethicone; POLYGLYCERYL-4 ISOSTEARATE; CETOSTEARYL ALCOHOL; POLYOXYL 40 CASTOR OIL; HEXYL LAURATE; .ALPHA.-TOCOPHEROL ACETATE, D-; HYALURONATE SODIUM; ALLANTOIN; SODIUM ASCORBATE; PHENOXYETHANOL; METHYLPARABEN; PROPYLPARABEN; ISOPROPYLPARABEN; ISOBUTYLPARABEN; LINALOOL, (+/-)- 

ACTIVE INGREDIENT

Octinoxate (7.5%) , Avobenzone (2.0%)

WARNINGS

FOR EXTERNAL USE ONLY. USE CARE DURING APPLICATION TO AVOID GETTING IN EYE. IF DISCOMFORT OR IRRITATIONDEVELOPS, WASH OFF GENTLY AND DISCONTINUE USE.

Keep out of reach of children.

INACTIVE INGREDIENT

Other Ingredients : Water , Ethylhexylmethoxycinnamate , Cyclopentasiloxane , Cetearyl Alcohol ,Dimethicone , Polyglyceryl-4 Isostearate , Cetyl PEG/PPG-10/1 Dimethicone ,

Hexyl Laurate , PEG-40 Castor Oil , Dromiceius (Emu) Oil , Potassium Cetyl Phosphate ,Tocopheryl Acetate ,Polysorbate 60 , Sodium Hyaluronate , Allantoin ,Sodium Ascorbate , Phenoxyethanol ,Methylparaben , Tetrasodium EDTA ,Carbomer , Isopropylparaben , Isobutylparaben ,Butylpraben , Sodium Dehydroacetate , Aminomethyl Propanol ,Linalool , Propylparaben , Acrylates/C10-C30 Alkyl Acrylate Crosspolymer